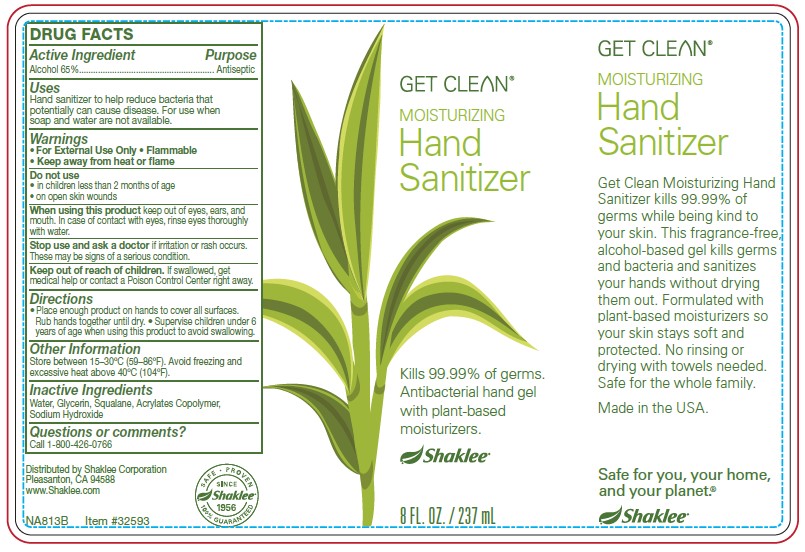 DRUG LABEL: Get Clean Moisturizing Hand Sanitizer
NDC: 59899-050 | Form: GEL
Manufacturer: Shaklee Corporation
Category: otc | Type: HUMAN OTC DRUG LABEL
Date: 20200601

ACTIVE INGREDIENTS: ALCOHOL 65 mL/100 mL
INACTIVE INGREDIENTS: WATER; GLYCERIN; SQUALANE; ETHYL ACRYLATE; SODIUM HYDROXIDE

ACTIVE INGREDIENT

Alcohol 65%. Purpose: Antiseptic

INDICATIONS AND USAGE

Hand sanitizer to help reduce bacteria that potentially can cause disease. For use wehn soap and water are not available.

WARNINGS

For external use only. Flamable. Keep away from heat or flame.

DO NOT USE

- On children less than 2 months of age
- On open skin wounds

WHEN USING

Keep out of eyes, ears, and mouth. In case of contact with eyes, rinse eyes thoroughly with water.

Stop use and ask a doctor if irritation or rash occurs. These may be signs of a serious condition.

Stop use and ask a doctor if irritation or rash occurs. These may be signs of a serious condition.

Keep out of reach of children. If swallowed, get medical help or contact a Poison Control Center right away.

Directions

- Place enough product on hands to cover all surfaces. Rub hands together until dry.
- Supervise children under 6 years of age when using this product to avoid swallowing.

Other Information

- Store between 15-30°C (59-86°F).
- Avoid freezing and excessive heat above 40°C (104°F)

INACTIVE INGREDIENT

Water, Glycerine, Squalane, Acrylates Copolymer, Sodium Hydroxide

Questions of Comments

Call 1-800-426-0766

PURPOSE

Hand sanitizer to help reduct bacteria that potentially can cause disease. For use when soap and water are not available.

DOSAGE AND ADMINISTRATION

Place enough product on hands to cover all surfaces. Rub hands together until dry.

PACKAGE LABEL

237 mL NDC: 59899-050-01